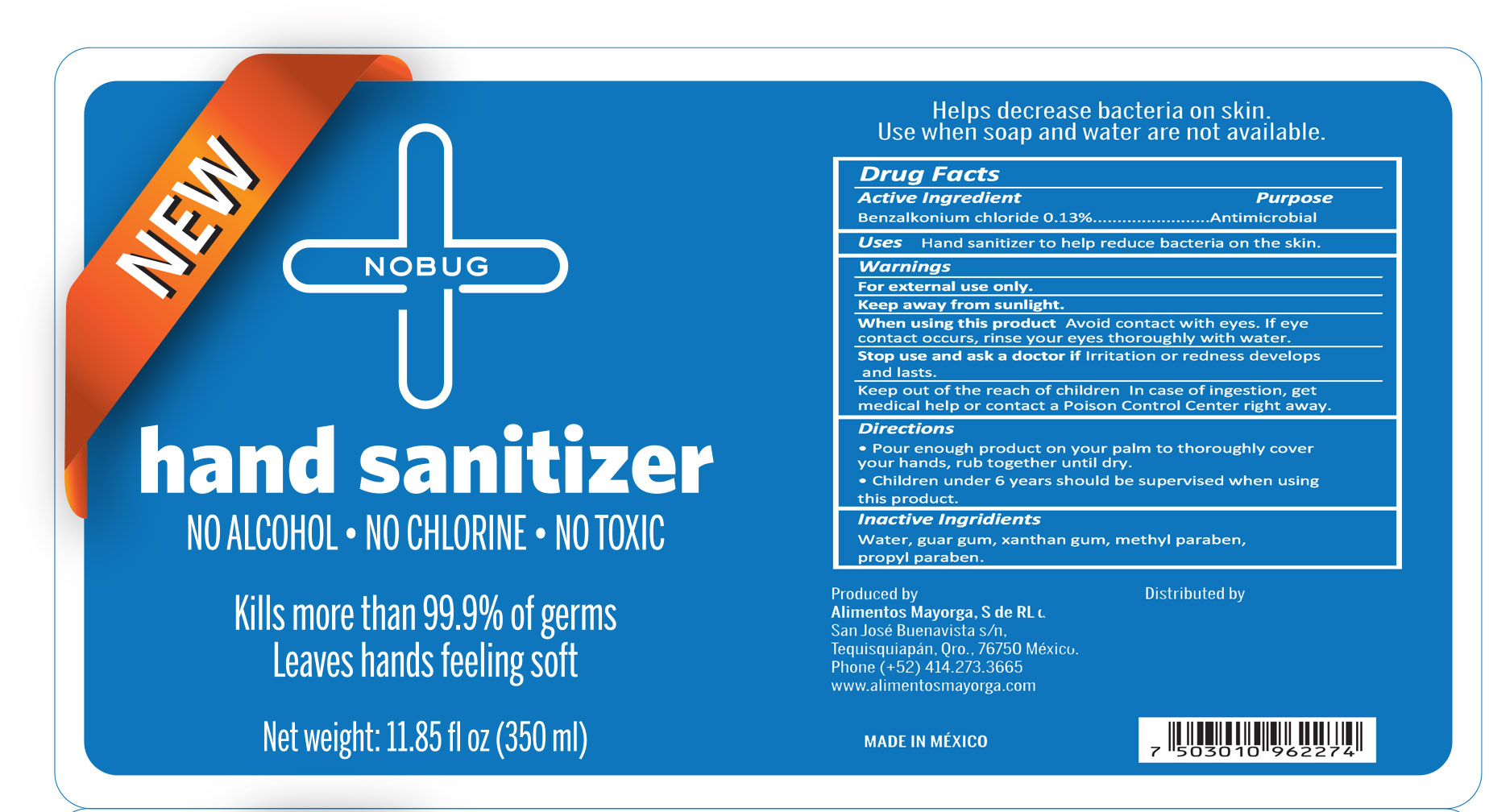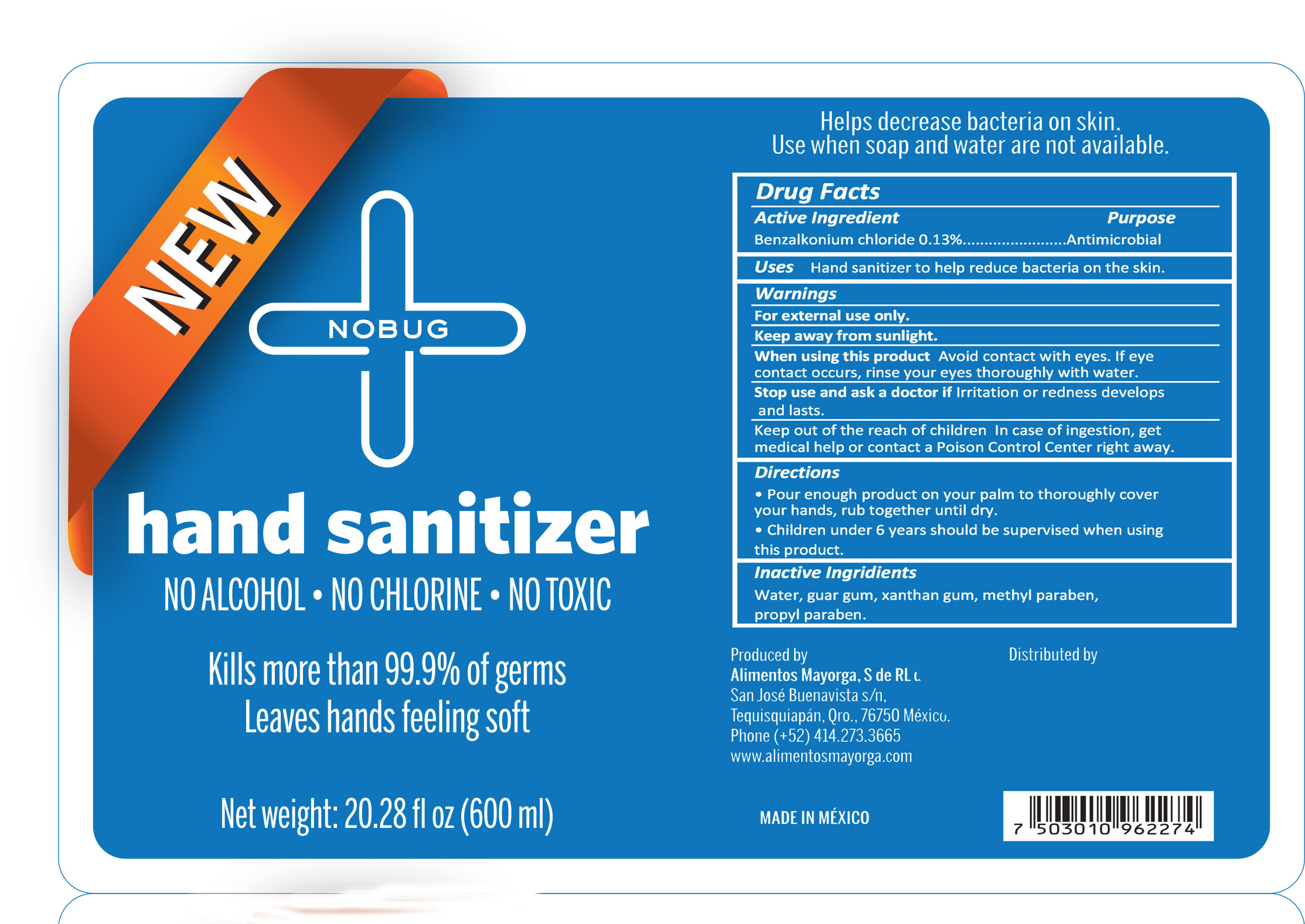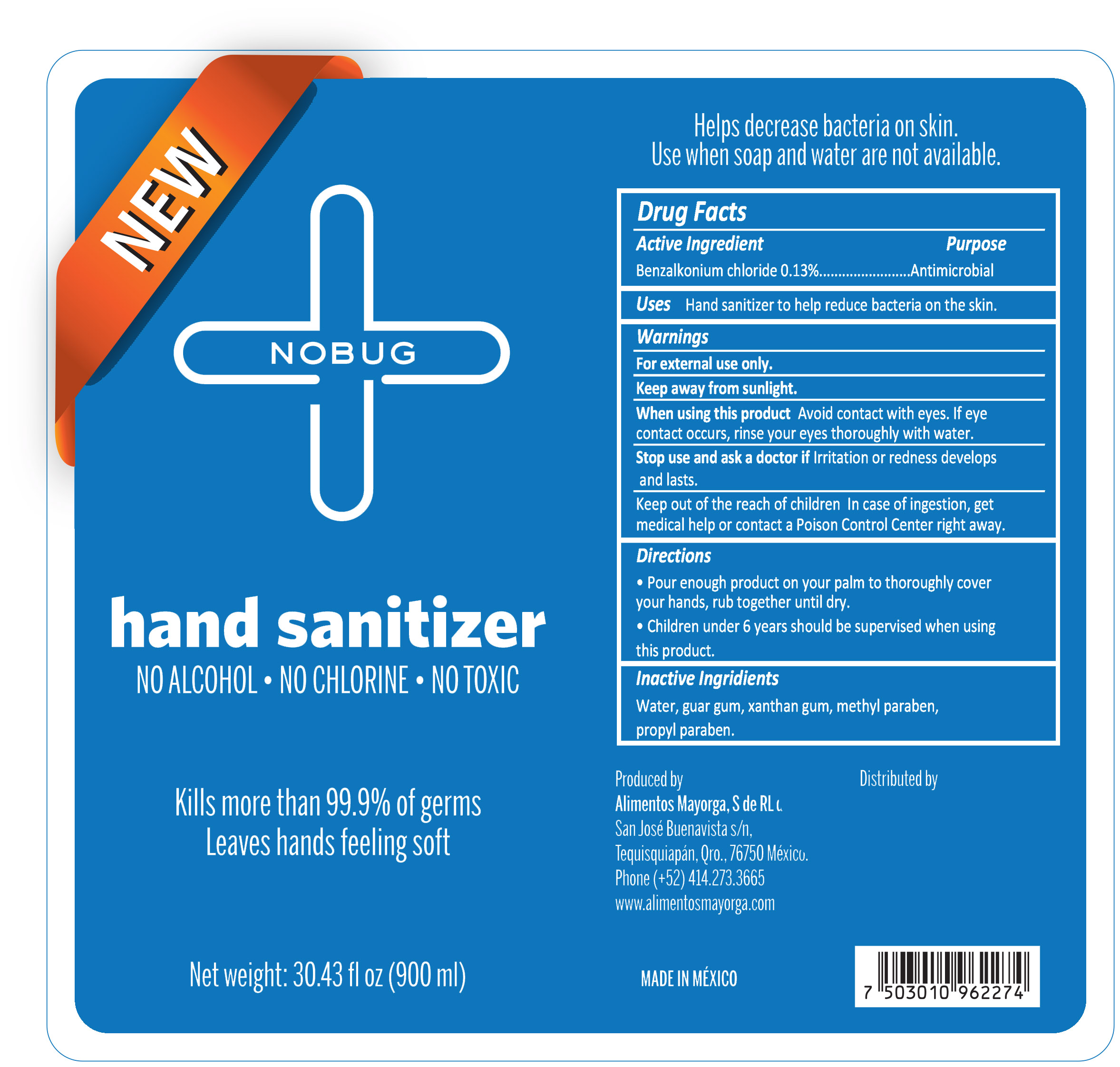 DRUG LABEL: NON-ALCOHOL HAND SANITIZER
NDC: 77686-001 | Form: LIQUID
Manufacturer: ALIMENTOS MAYORGA S DE RL DE CV
Category: otc | Type: HUMAN OTC DRUG LABEL
Date: 20200714

ACTIVE INGREDIENTS: BENZALKONIUM CHLORIDE 0.13 g/100 mL
INACTIVE INGREDIENTS: GUAR GUM; METHYLPARABEN; PROPYLPARABEN; WATER; XANTHAN GUM

Active Ingredient

Benzalkonium chloride 0.13%

Purpose

Antimicrobial

Warnings

For external use only.

Keep away from sunlight.

When using this product

Avoid contact with eyes. If eye contact occurs, rinse your eyes throughly with water.

Stop Use

Stop use if irritayion or redness developsnd lasts.

Ask doctor

Ask doctor if irritation or redness develops and lasts.

Keep out of reach of children

Directions

Pour enough product on your palm to thoroughly cover your hands, rub together until dry.

Children under 6 years should be supervised when using this product.

Inactive Ingridients

Water, guar gum, xanthan gum, methyl paraben, propyl paraben,

Uses

Hand sanitizer to help reduce bacteria on the skin.

HAND SANITIZER

NO ALCOHOL NO CHOLRINE NO TOXIC

Kills more then 99.9% of the germs

Leaves hands feeling soft